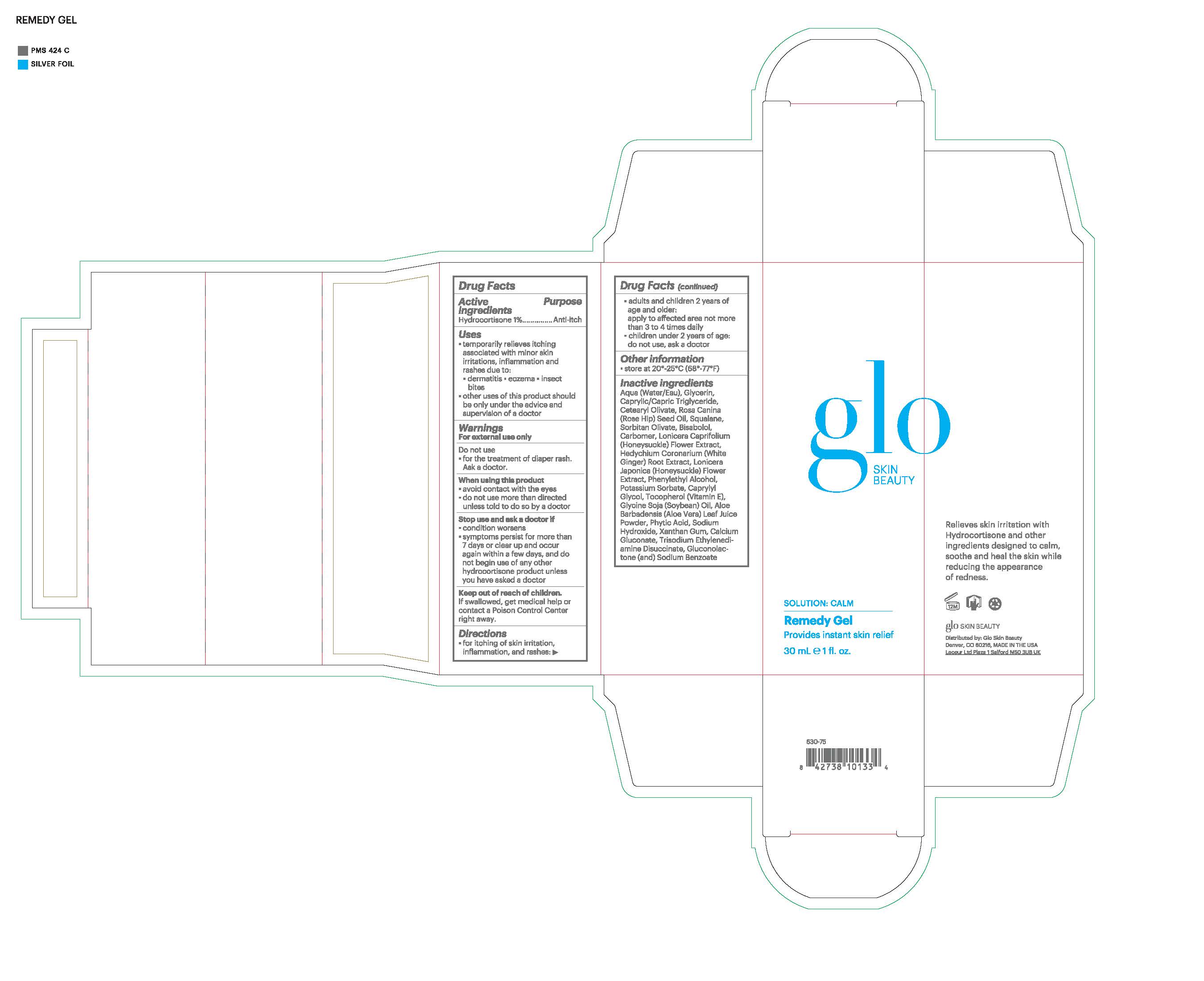 DRUG LABEL: glo SKIN BEAUTY Remedy Gel
NDC: 60541-1900 | Form: GEL
Manufacturer: Hayden Caleel LLC
Category: otc | Type: HUMAN OTC DRUG LABEL
Date: 20250105

ACTIVE INGREDIENTS: HYDROCORTISONE 1 g/100 g
INACTIVE INGREDIENTS: GLYCERIN; WATER; CAPRYLIC/CAPRIC ACID; ROSA CANINA FRUIT OIL; SQUALANE; SORBITAN OLIVATE; .ALPHA.-BISABOLOL, (+)-; CARBOMER 940; GLUCONOLACTONE; LONICERA CAPRIFOLIUM FLOWER; HEDYCHIUM CORONARIUM ROOT; LONICERA JAPONICA FLOWER; SODIUM BENZOATE; POTASSIUM SORBATE; CAPRYLYL GLYCOL; TOCOPHEROL; SOYBEAN OIL; ALOE VERA WHOLE; SODIUM HYDRIDE; XANTHAN GUM; TRISODIUM ETHYLENEDIAMINE DISUCCINATE

DRUG FACTS

Active Ingredients

Hydrocortisone 1%

Purpose

Anti-itch

Uses

- temporarily relieves itching associate with minor skin irritations, inflammation an rashes due to:
- dermatitis, exzema, insect bites
- other uses of this prouct should be only under the advice and supervision of a doctor

Warnings

For external use only

Do not use

- for the treatment of iaper rash. Ask a doctor

When using this product
• avoid contact with the eyes
• do not use more than directed unless told to do so by a doctor

Stop use and ask a doctor if

- condition worsens
- symptoms persist for more than 7 days or clear up and occur again within a few days, and do not begin use of any other hyrdrocortisone product unless you have asked a doctor

Keep out of reach of children. If swallowed, get medical help
or contact a Poison Control Center right away.

Directions

- for itching of skin irritation, inflamation and rashes
- adults an chilren 2 years of age and older: apply to affected area not more than 3 to 4 times daily
- children under 2 years of age: do not use, ask a doctor

Inactive Ingredients

Aqua (Water), Glycerin, Caprylic/Capric Triglyceride, Cetearyl Olivate, Rosa Canina (Rose Hip) Fruit Oil, Squalane, Sorbitan Olivate, Bisabolol, Carbomer, Gluconolactone, Lonicera Caprifolium (Honeysuckle) Flower Extract, Hedychium Coronarium (White Ginger) Root Extract, Lonicera Japonica (Honeysuckle) Flower Extract, Sodium Benzoate, Phenethyl Alcohol, Potassium Sorbate, Caprylyl Glycol, Tocopherol, Glycine Soja (Soybean) Oil, Aloe Barbadensis Leaf Juice Powder, Phytic Acid, Sodium Hydroxide, Xanthan Gum, Trisodium Ethylenediamine Disuccinate